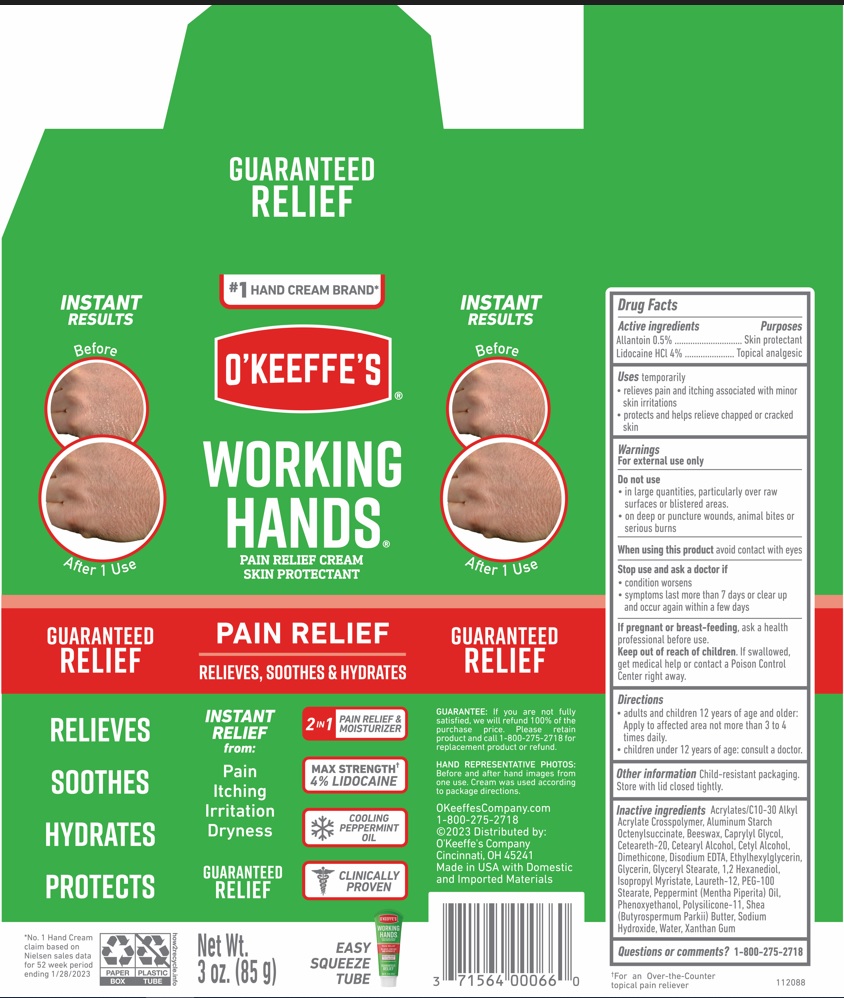 DRUG LABEL: OKeeffes Working Hands Pain Relief
NDC: 71564-009 | Form: CREAM
Manufacturer: The Gorilla Glue Company/O'Keeffe's Company
Category: otc | Type: HUMAN OTC DRUG LABEL
Date: 20250101

ACTIVE INGREDIENTS: ALLANTOIN 0.5 g/100 g; LIDOCAINE HYDROCHLORIDE 4 g/100 g
INACTIVE INGREDIENTS: 1,2-HEXANEDIOL; ETHYLHEXYLGLYCERIN; ISOPROPYL MYRISTATE; GLYCERYL 1-STEARATE; PEPPERMINT OIL; SHEA BUTTER; ALUMINUM STARCH OCTENYLSUCCINATE; POLYOXYL 20 CETOSTEARYL ETHER; LAURETH-12; CAPRYLYL GLYCOL; CETOSTEARYL ALCOHOL; DODECAMETHYLPENTASILOXANE; DIMETHICONE/VINYL DIMETHICONE CROSSPOLYMER (SOFT PARTICLE); SODIUM HYDROXIDE; CARBOMER INTERPOLYMER TYPE B (ALLYL PENTAERYTHRITOL CROSSLINKED); EDETATE DISODIUM ANHYDROUS; GLYCERIN; PEG-100 STEARATE; CETYL ALCOHOL; PHENOXYETHANOL; XANTHAN GUM; WHITE WAX; WATER

O’Keeffe’s Working Hands Pain Relief Cream Skin Protectant

Active ingredients . . . . . . . . . . . . . Purposes

Allantoin 0.5% . . . . . . . . . . . . . . . . Skin protectant

Lidocaine HCl 4% . . . . . . . . . . . . . Topical analgesic

Purposes

Uses

temporarily

- relieves pain and itching associated with minor skin irritations
- protects and helps relieve chapped or cracked skin

Warnings

For external use only

Do not use

- in large quantities, particularly over raw surfaces or blistered areas.
- on deep or puncture wounds, animal bites or serious burns

When using this product avoid contact with eyes

Stop use and ask a doctor if

- condition worsens
- symptoms last more than 7 days or clear up and occur again within a few days

PREGNANCY OR BREAST FEEDING

If pregnant or breast-feeding, ask a health professional before use.

Keep out of reach of children. If swallowed, get medical help or contact a Poison Control Center right away.

Directions

- adults and children 12 years of age and older: Apply to affected area not more than 3 to 4 times daily.
- children under 12 years of age: consult a doctor.

Other information

Child-resistant packaging. Store with lid closed tightly.

Inactive ingredients

Acrylates/C10-30 Alkyl Acrylate Crosspolymer, Aluminum Starch Octenylsuccinate, Beeswax, Caprylyl Glycol, Ceteareth-20, Cetearyl Alcohol, Cetyl Alcohol, Dimethicone, Disodium EDTA, Ethylhexylglycerin, Glycerin, Glyceryl Stearate, 1,2 Hexanediol, Isopropyl Myristate, Laureth-12, PEG-100 Stearate, Peppermint (Mentha Piperita) Oil, Phenoxyethanol, Polysilicone-11, Shea (Butyrospermum Parkii) Butter, Sodium Hydroxide, Water, Xanthan Gum

Questions or comments?

1-800-275-2718

O'KEEFFE'S® WORKING HANDS®

PAIN RELIEF CREAM SKIN PROTECTANT

PAIN RELIEF

RELIEVES, SOOTHES & HYDRATES

INSTANT RELIEF from:

Pain

Itching Irritation

Dryness

2 IN 1 PAIN RELIEF & MOISTURIZER

MAX STRENGTH† 4% LIDOCAINE

COOLING PEPPERMINT OIL

CLINICALLY PROVEN

RELIEVES

SOOTHES

HYDRATES

PROTECTS

PACKAGE LABEL

OKEEFFE'S® WORKING HANDS®

PAIN RELIEF CREAM SKIN PROTECTANT

Net Wt. 3 oz (85 g)

OKeeffesCompany.com

1-800-275-2718

©2023 Distributed by:

O'Keeffe's Company

Cincinnati, OH 45241

Made in USA with Domestic and Imported Materials